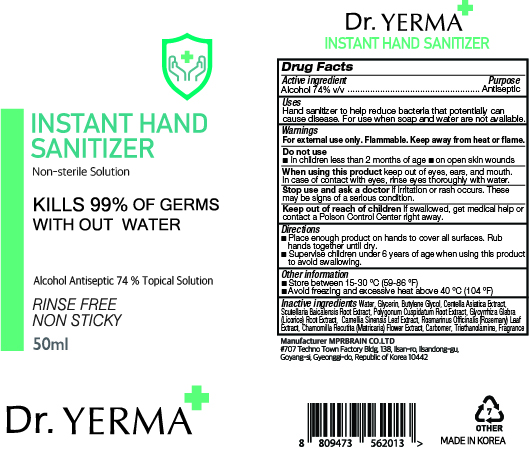 DRUG LABEL: Dr. YERMA INSTANT HAND SANITIZER
NDC: 74741-0050 | Form: GEL
Manufacturer: MPRBRAIN CO.LTD
Category: otc | Type: HUMAN OTC DRUG LABEL
Date: 20200406

ACTIVE INGREDIENTS: ALCOHOL 37 mL/50 mL
INACTIVE INGREDIENTS: ROSEMARY; CARBOMER HOMOPOLYMER, UNSPECIFIED TYPE; GREEN TEA LEAF; GLYCYRRHIZA GLABRA; GLYCERIN; BUTYLENE GLYCOL; WATER; CENTELLA ASIATICA; SCUTELLARIA BAICALENSIS ROOT; POLYGONUM CUSPIDATUM ROOT; CHAMOMILE; TROLAMINE

Dr. YERMA INSTANT HAND SANITIZER 50 ml : 74741-0050-1